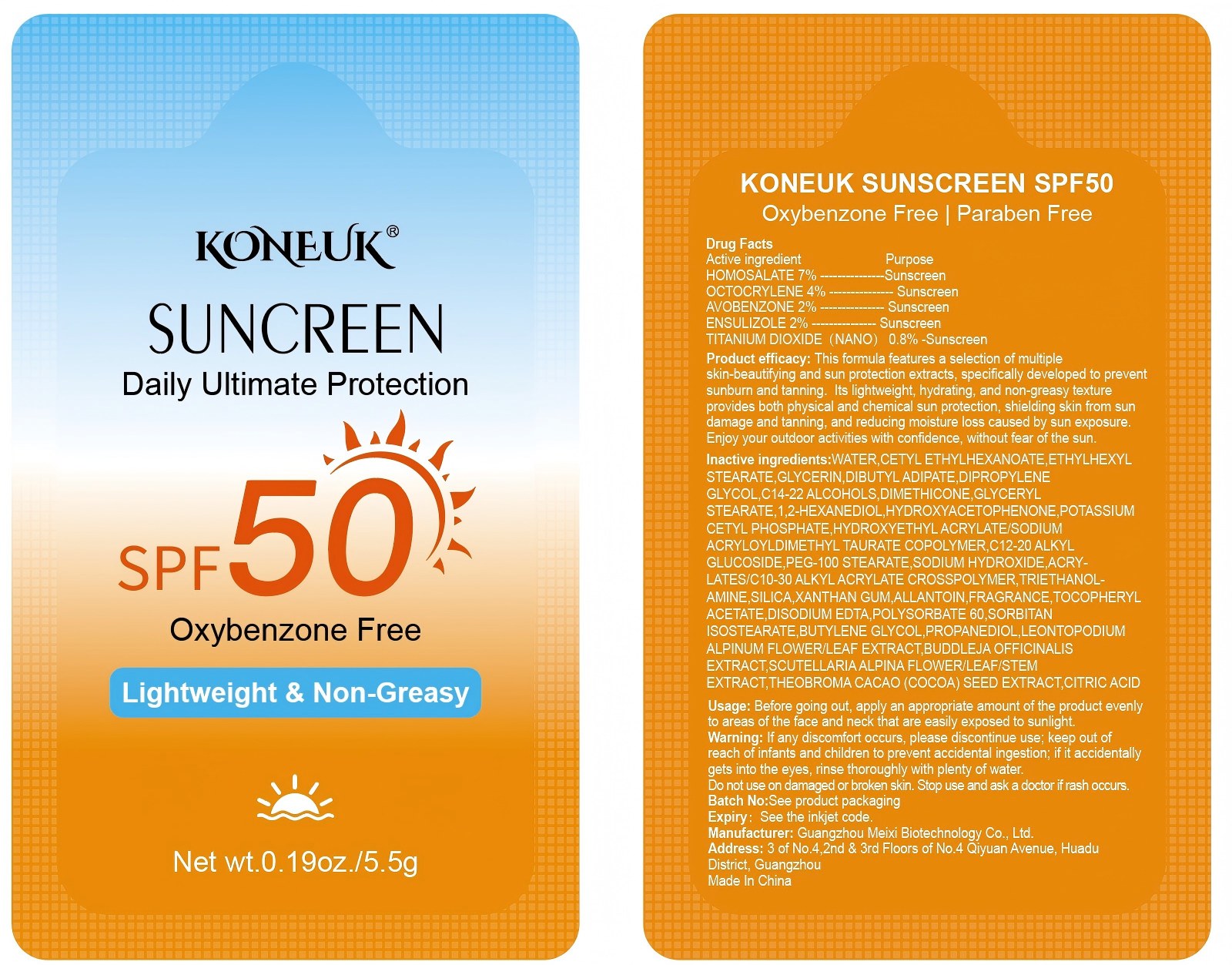 DRUG LABEL: KONEUK SUNSCREEN SPF50
NDC: 84167-323 | Form: CREAM
Manufacturer: Guangzhou Meixi Biotechnology Co., Ltd.
Category: otc | Type: HUMAN OTC DRUG LABEL
Date: 20260120

ACTIVE INGREDIENTS: OCTOCRYLENE 1 g/1 1; HOMOSALATE 1 g/1 1; TITANIUM DIOXIDE 1 g/1 1; AVOBENZONE 1 g/1 1; ENSULIZOLE 1 g/1 1
INACTIVE INGREDIENTS: PROPANEDIOL; TRIETHANOLAMINE; C12-20 ALKYL GLUCOSIDE; GLYCERIN; 2-BROMO-4'-HYDROXYACETOPHENONE; SORBITAN ISOSTEARATE; CITRIC ACID; ACRYLATES/C10-30 ALKYL ACRYLATE CROSSPOLYMER (60000 MPA.S); ETHYLHEXYL STEARATE; FRAGRANCE 13576; DIBUTYL ADIPATE; POTASSIUM CETYL PHOSPHATE; PEG-100 STEARATE; CETYL ETHYLHEXANOATE; CALCIUM DISODIUM EDTA; DISODIUM ALPHA-TOCOPHERYL PHOSPHATE, DL-; BUTYLENE GLYCOL; ALLANTOIN; GLYCERYL STEARATE; XANTHAN GUM; WATER; DIPROPYLENE GLYCOL; C14-22 ALCOHOLS; 1,2-HEXANEDIOL; SODIUM HYDROXIDE; POLYSORBATE 60; HYDROXYETHYL ACRYLATE/SODIUM ACRYLOYLDIMETHYL TAURATE COPOLYMER (45000 MPA.S AT 1%)

ACTIVE INGREDIENT

HOMOSALATE,OCTOCRYLENE,AVOBENZONE,ENSULIZOLE,TITANIUM DIOXIDE

keep out of reach of children section

PURPOSE

Sunscreen

WARNINGS

keep out reach of children

INACTIVE INGREDIENT

WATER,CETYL ETHYLHEXANOATE,ETHYLHEXYL STEARATE,GLYCERIN,DIBUTYL ADIPATE,DIPROPYLENE GLYCOL

DOSAGE AND ADMINISTRATION

Apply to the palms, rub onto the skin, used for sun protection

INDICATIONS AND USAGE

Apply to the palms, rub onto the skin, used for sun protection